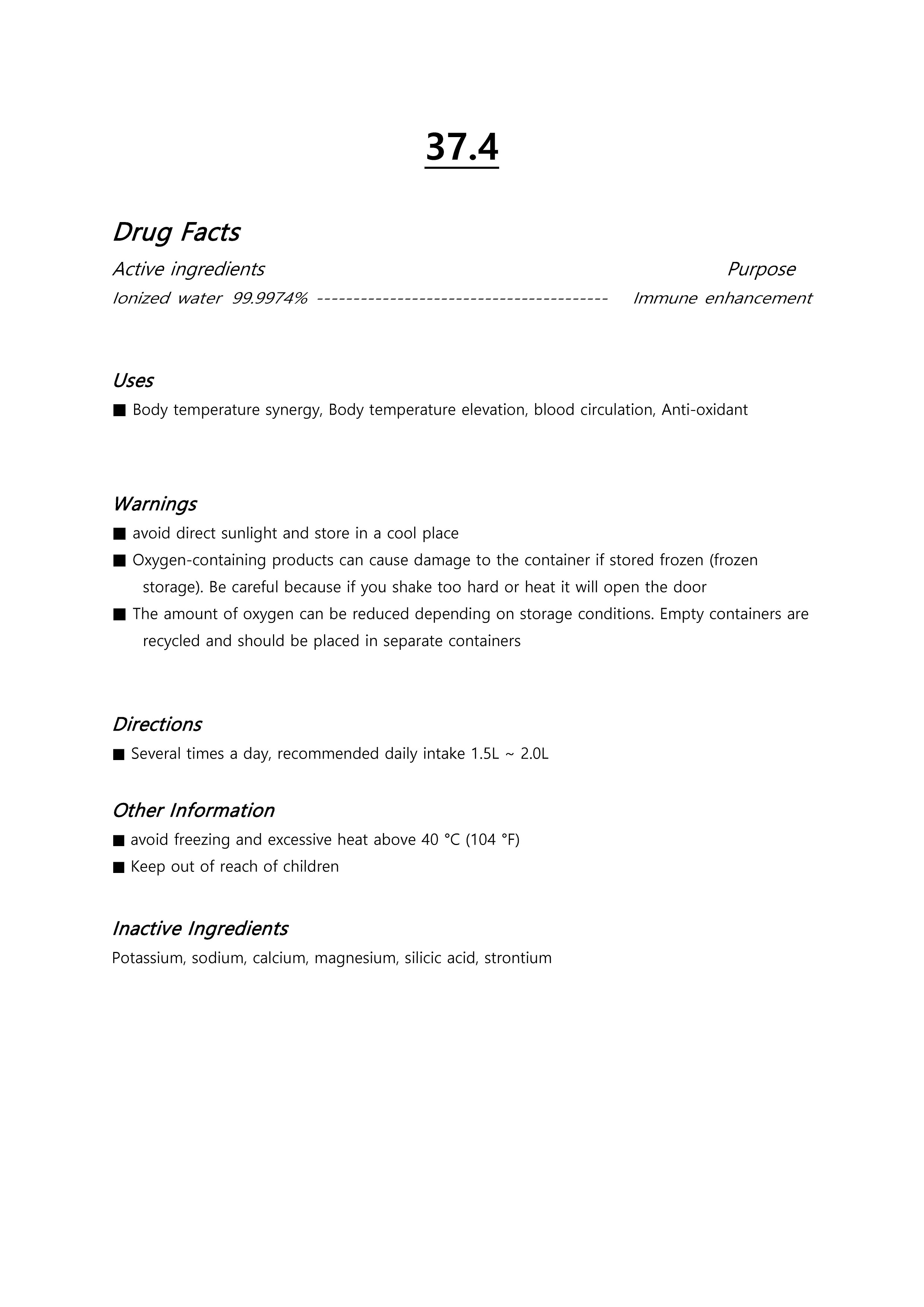 DRUG LABEL: 37.4
NDC: 71631-0003 | Form: LIQUID
Manufacturer: Jesus Glory Bio Co.,Ltd.
Category: otc | Type: HUMAN OTC DRUG LABEL
Date: 20220126

ACTIVE INGREDIENTS: WATER 99.9974 g/100 mL
INACTIVE INGREDIENTS: OXYGEN

Drug Facts

ACTIVE INGREDIENT

Water

INACTIVE INGREDIENT

Oxygen

PURPOSE

Drinking the processed water

keep out of reach of the children

INDICATIONS AND USAGE

drink processed water

WARNINGS

Avoid direct sunlight and store in a cool place.
Zone Due to the nature of the product containing oxygen, the container may be damaged if it is frozen (stored frozen).
Be careful because if you shake too hard or apply heat, the lid may open.

DOSAGE AND ADMINISTRATION

The amount of oxygen may be reduced depending on the storage condition.The amount of oxygen may be reduced depending on the storage condition.